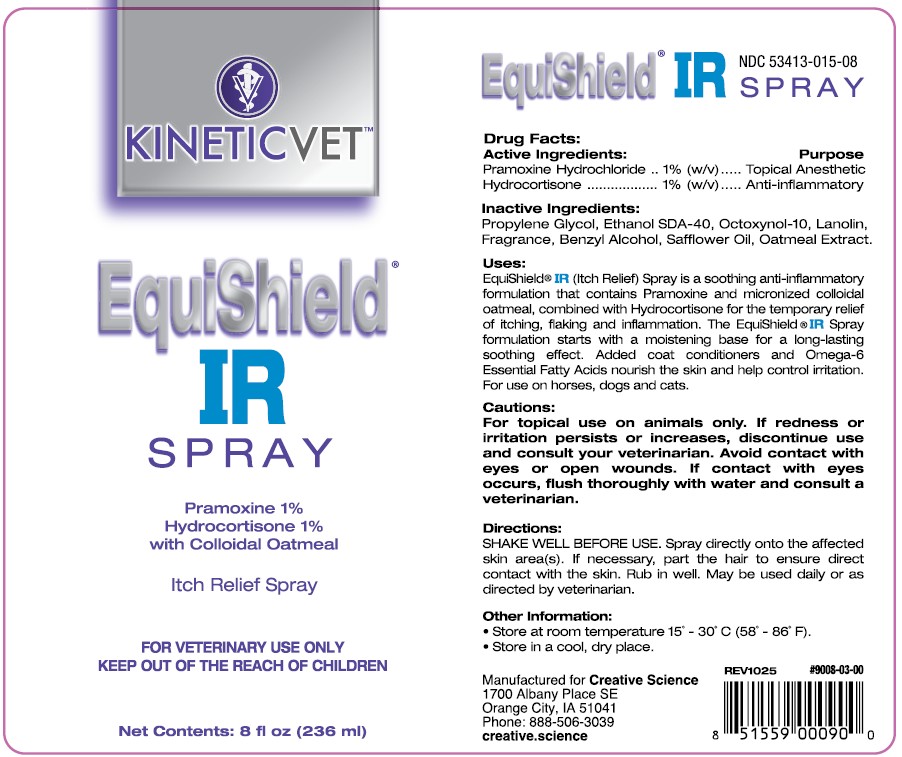 DRUG LABEL: EquiShield IR
NDC: 53413-015 | Form: SPRAY
Manufacturer: Creative Science
Category: animal | Type: OTC ANIMAL DRUG LABEL
Date: 20251229

ACTIVE INGREDIENTS: PRAMOXINE 10 mg/1 mL; HYDROCORTISONE 10 mg/1 mL

EquiShield IR SPRAY

NDC 53413-015-08

Drug Facts: Active Ingredients:

Pramoxine Hydrochloride .....1% (w/v)
Hydrocortisone .................. 1% (w/v)

Purpose

Topical Anesthetic

Anti-Inflammatory

Inactive Ingredients:

Propylene Glycol, Ethanol SDA-40, Octoxynol-10, Lanolin, Fragrance, Benzyl Alcohol, Safflower Oil, Oatmeal Extract.

Uses:

EquiShield® IR (Itch Relief) Spray is a soothing anti-inflammatory formulation that contains Pramoxine and micronized colloidal oatmeal, combined with Hydrocortisone for the temporary relief of itching, flaking and inflammation. The EquiShield® IR Spray formulation starts with a moistening base for a long-lasting soothing effect. Added coat conditioners and Omega-6 Essential Fatty Acids nourish the skin and help control irritation. For use on horses, dogs and cats.

Cautions:

For topical use on animals only. If redness or irritation persists or increases, discontinue use and consult your veterinarian. Avoid contact with eyes or open wounds. If contact with eyes occurs, flush thoroughly with water and consult a veterinarian.

Directions:

SHAKE WELL BEFORE USE. Spray directly onto the affected skin area(s). If necessary, part the hair to ensure direct contact with the skin. Rub in well. May be used daily or as directed by veterinarian.

Other Information:

• Store at room temperature 15° - 30° C (58° - 86° F).
• Store in a cool, dry place.

REV1025 #9008-03-00 UPC 851559000900

Manufactured for Creative Science

1700 Albany Place SE

Orange City, IA 51041

Phone: 888-506-3039

creative.science

PACKAGE LABEL

EquiShield®

IR

SPRAY

Pramoxine 1%

Hydrocortisone 1%

with Colloidal Oatmeal

Itch Relief Spray

FOR VETERINARY USE ONLY

KEEP OUT OF THE REACH OF CHILDREN

Net Contents: 8 fl oz. (236 mL)